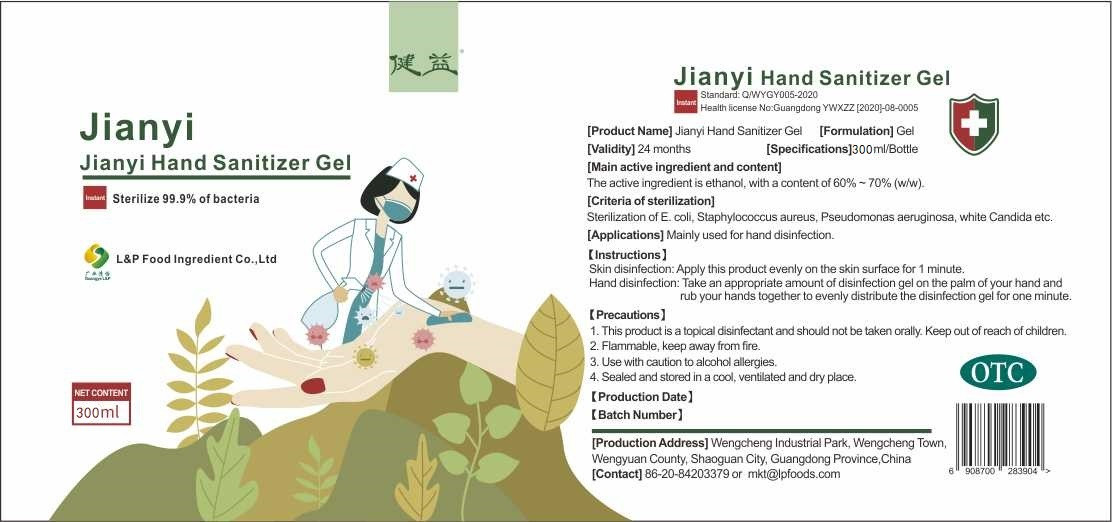 DRUG LABEL: jianyi Hand Sanitizer Gel
NDC: 54380-003 | Form: GEL
Manufacturer: L&P Food Ingredient Co., Ltd.
Category: otc | Type: HUMAN OTC DRUG LABEL
Date: 20200424

ACTIVE INGREDIENTS: ALCOHOL 298.5 mL/300 mL
INACTIVE INGREDIENTS: CARBOMER HOMOPOLYMER, UNSPECIFIED TYPE

DOSAGE AND ADMINISTRATION

Sealed and stored in a cool. venillated and dry place.

INACTIVE INGREDIENT

carbomer

INDICATIONS AND USAGE

Skin disinfection: Apply this product evenly on the skin surface for 1 minute.
Hand disinfection: Take an appropriate amount of disinfection gel on the paim of your hand and rub your hands together to evenly distrbute the disinfection gel for one minute.

ACTIVE INGREDIENT

ethyl alcohol

keep out of children

PURPOSE

Disinfection
Sterilization

WARNINGS

1. This product is a topical disinfectant and should not be taken orally Keep out of reach of children.
2. Flammable, keep away from fire.
3. Use with caution to alcohol alegies.
4. Sealed and stored in a cool. venillated and dry place.